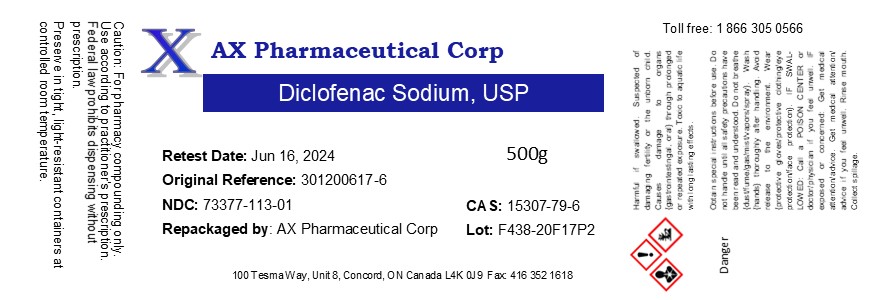 DRUG LABEL: Diclofenac sodium
NDC: 73377-113 | Form: POWDER
Manufacturer: AX Pharmaceutical Corp
Category: other | Type: BULK INGREDIENT
Date: 20210602

ACTIVE INGREDIENTS: DICLOFENAC SODIUM 1 g/1 g

Diclofenac sodium